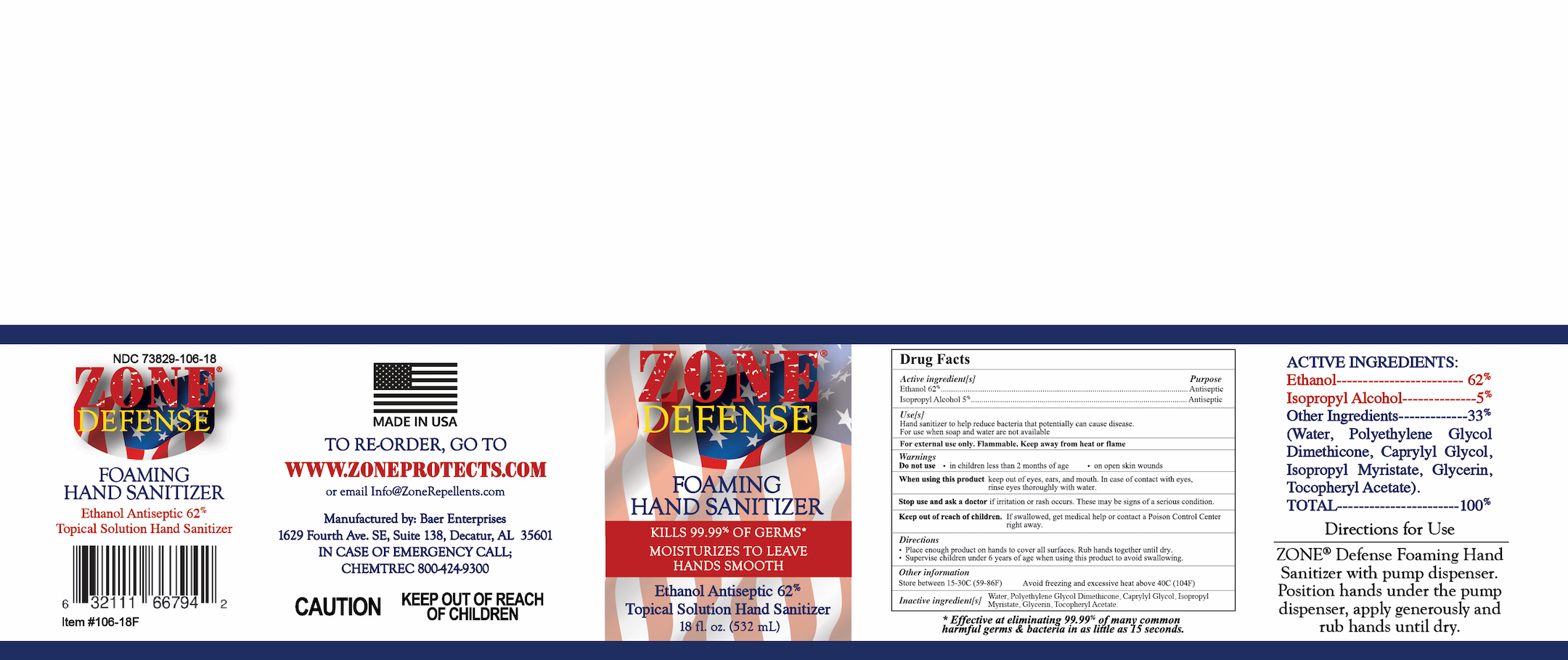 DRUG LABEL: Zone Defense Foaming Hand Sanitizer
NDC: 73829-101 | Form: LIQUID
Manufacturer: Baer Enterprises, LLC
Category: otc | Type: HUMAN OTC DRUG LABEL
Date: 20220124

ACTIVE INGREDIENTS: ISOPROPYL ALCOHOL 5 mL/100 mL; ALCOHOL 62 mL/100 mL
INACTIVE INGREDIENTS: CAPRYLYL GLYCOL 1 mL/100 mL; PEG-12 DIMETHICONE 5 mL/100 mL; ALPHA-TOCOPHEROL ACETATE 0.5 mL/100 mL; ISOPROPYL MYRISTATE 1 mL/100 mL; GLYCERIN 0.5 mL/100 mL; WATER 25 mL/100 mL

Active Ingredient(s)

Ethanol 62% v/v. Purpose: Antiseptic

Isopropyl Alcohol 5% v/v. Purpose: Antiseptic

Purpose

Antiseptic, Hand Sanitizer

Use

Hand Sanitizer to help reduce bacteria that potentially can cause disease. For use when soap and water are not available.

Warnings

For external use only. Flammable. Keep away from heat or flame

Do not use

- in children less than 2 months of age
- on open skin wounds

When using this product keep out of eyes, ears, and mouth. In case of contact with eyes, rinse eyes thoroughly with water.
Stop use and ask a doctor if irritation or rash occurs. These may be signs of a serious condition.
Keep out of reach of children. If swallowed, get medical help or contact a Poison Control Center right away.

Stop use and ask a doctor if irritation or rash occurs. These may be signs of a serious condition.

Keep out of reach of children. If swallowed, get medical help or contact a Poison Control Center right away.

Directions

- Place enough product on hands to cover all surfaces. Rub hands together until dry.
- Supervise children under 6 years of age when using this product to avoid swallowing.

Other information

- Store between 15-30C (59-86F)
- Avoid freezing and excessive heat above 40C (104F)

Inactive ingredients

Water, Polyethylene Glycol Dimethicone, Caprylyl Glycol, Isopropyl Myristate, Glycerin, Tocopheryl Acetate

Package Label - Principal Display Panel

18 fl. oz. (532 mL) NDC 73829-101-18